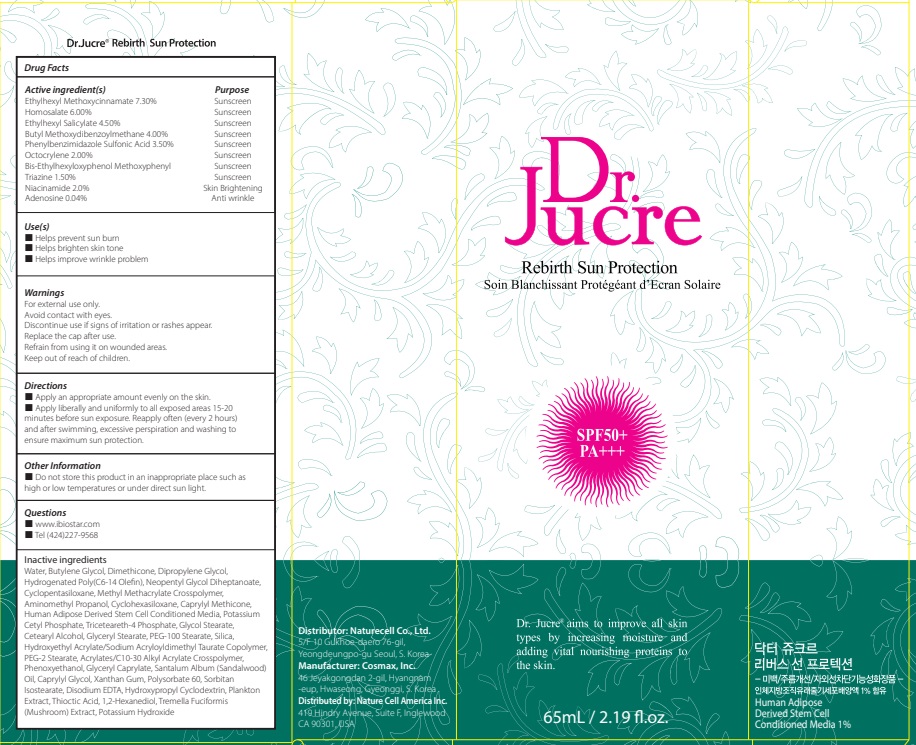 DRUG LABEL: Dr.Jucre Rebirth Sun Protection
NDC: 83071-150 | Form: CREAM
Manufacturer: NATURECELL CO., LTD.
Category: otc | Type: HUMAN OTC DRUG LABEL
Date: 20250102

ACTIVE INGREDIENTS: OCTINOXATE 7.3 g/100 mL; HOMOSALATE 6 g/100 mL; OCTISALATE 4.5 g/100 mL; AVOBENZONE 4 g/100 mL; ENSULIZOLE 3.5 g/100 mL; OCTOCRYLENE 2 g/100 mL; BEMOTRIZINOL 1.5 g/100 mL; NIACINAMIDE 2 g/100 mL; ADENOSINE 0.04 g/100 mL
INACTIVE INGREDIENTS: WATER; BUTYLENE GLYCOL; DIMETHICONE

ACTIVE INGREDIENTS

Ethylhexyl Methoxycinnamate 7.30%
Homosalate 6.00%
Ethylhexyl Salicylate 4.50%
Butyl Methoxydibenzoylmethane 4.00%
Phenylbenzimidazole Sulfonic Acid 3.50%
Octocrylene 2.00%
Bis-Ethylhexyloxyphenol Methoxyphenyl Triazine 1.50%
Niacinamide 2.0%
Adenosine 0.04%

INACTIVE INGREDIENTS

Water, Butylene Glycol, Dimethicone, Dipropylene Glycol, Hydrogenated Poly(C6-14 Olefin), Neopentyl Glycol Diheptanoate, Cyclopentasiloxane, Methyl Methacrylate Crosspolymer, Aminomethyl Propanol, Cyclohexasiloxane, Caprylyl Methicone, Human Adipose Derived Stem Cell Conditioned Media, Potassium Cetyl Phosphate, Triceteareth-4 Phosphate, Glycol Stearate, Cetearyl Alcohol, Glyceryl Stearate, PEG-100 Stearate, Silica, Hydroxyethyl Acrylate/Sodium Acryloyldimethyl Taurate Copolymer, PEG-2 Stearate, Acrylates/C10-30 Alkyl Acrylate Crosspolymer, Phenoxyethanol, Glyceryl Caprylate, Santalum Album (Sandalwood) Oil, Caprylyl Glycol, Xanthan Gum, Polysorbate 60, Sorbitan Isostearate, Disodium EDTA, Hydroxypropyl Cyclodextrin, Plankton Extract, Thioctic Acid, 1,2-Hexanediol, Tremella Fuciformis (Mushroom) Extract, Potassium Hydroxide

PURPOSE

Sunscreen
Sunscreen
Sunscreen
Sunscreen
Sunscreen
Sunscreen
Sunscreen
Skin Brightening
Anti wrinkle

WARNINGS

For external use only.
Avoid contact with eyes.
Discontinue use if signs of irritation or rashes appear.
Replace the cap after use.
Refrain from using it on wounded areas.
Keep out of reach of children.

KEEP OUT OF REACH OF CHILDREN

Keep out of the reach of children.

Uses

■ Helps prevent sun burn
■ Helps brighten skin tone
■ Helps improve wrinkle problem

Directions

■ Apply an appropriate amount evenly on the skin.
■ Apply liberally and uniformly to all exposed areas 15-20 minutes before sun exposure. Reapply often (every 2 hours) and after swimming, excessive perspiration and washing to ensure maximum sun protection.

Other Information

■ Do not store this product in an inappropriate place such as high or low temperatures or under direct sun light.

Questions

■ www.ibiostar.com
■ Tel (424)227-9568